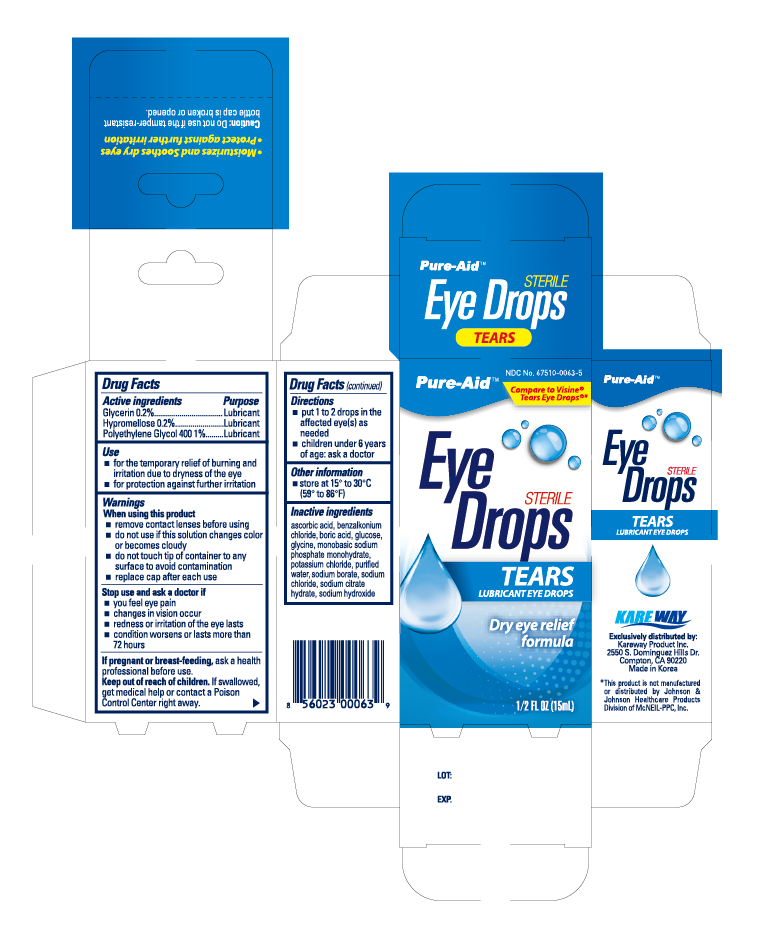 DRUG LABEL: Tears Lubricant
NDC: 67510-0063 | Form: LIQUID
Manufacturer: Kareway Product, Inc.
Category: otc | Type: HUMAN OTC DRUG LABEL
Date: 20191028

ACTIVE INGREDIENTS: GLYCERIN 2 mg/1 mL; HYPROMELLOSES 2 mg/1 mL; POLYETHYLENE GLYCOL 400 10 mg/1 mL
INACTIVE INGREDIENTS: BORIC ACID; ASCORBIC ACID; BENZALKONIUM CHLORIDE; DEXTROSE; MAGNESIUM CHLORIDE; POTASSIUM CHLORIDE; WATER; SODIUM BORATE; SODIUM CITRATE; SODIUM LACTATE

Pure-Aid Artificial Tears

Active Ingredient

Glycerin 0.2%

Hypromellose 0.2%

Polyethylene Glycol 400 1%

Purpose

Lubricant

Lubricant

Lubricant

Use

- for the temporary relief of burning and irritation due to dryness of the eye
- for protection against further irritation

Warnings

When using this product

- remove contact lenses before using
- do not use if this solution changes color or become cloudy
- do not touch tip of container to any surface to avoid contamination
- replace cap after each use

Stop use and ask a doctor if

- you feel eye pain
- changes in vision occur
- redness or irritation of the eye lasts
- condition worsens or lasts more than 72 hours

If pregnant or breast-feeding,

ask a health professional before use.

Keep out of reach of children.

If swallowed, get medical help or contact a Poison Control Center right away.

Directions

- Put 1 to 2 drops in the affected eye(s) up to 4 times daily
- children under 6 years of age: ask a doctor

Other information

- store between 15° to 25°C (59°F to 77°F)

Inactive ingredients

Ascorbic acid, benzalkonium chloride, boric acid, dextrose, magnesium chloride, potassium chloride, purified water, sodium borate, sodium chloride, sodium citrate, sodium lactate

Package principal display panel

Pureaid Artificial Tears